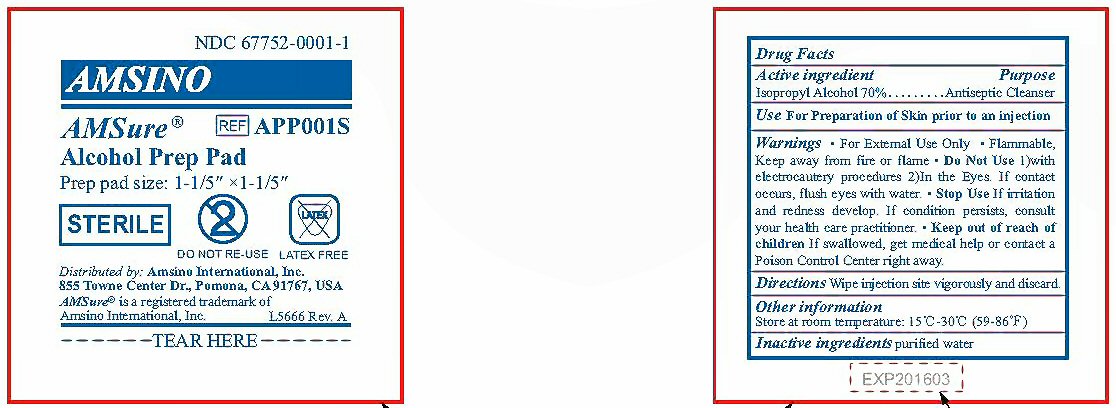 DRUG LABEL: AMSure
NDC: 67752-0001 | Form: SWAB
Manufacturer: Amsino International, Inc.
Category: otc | Type: HUMAN OTC DRUG LABEL
Date: 20120327

ACTIVE INGREDIENTS: ISOPROPYL ALCOHOL 0.7 mL/1 mL
INACTIVE INGREDIENTS: WATER

Active Ingredient Section

Drug Facts

Active ingredient

Isopropyl Alcohol 70%

Purpose Section

Purpose

Antiseptic Cleanser

Keep Out Of Reach Of Children Section

Keep out of reach of children. If swallowed, get medical help or contact a Poison Control Center right away.

Uses Section

Use For preparation of Skin prior to an injection.

Warnings Section

Warnings

- For External Use Only
- Flammable, Keep away from fire or flame
- Do Not Use 1) with electrocautery procedures 2) In the eyes. If contact occurs, flush eyes with water
- Stop Use If irritation and redness develop. If condition persists, contact your health care practitioner.
- Keep out of reach of children. If swallowed, get medical help or contact a Poison Control Center right away.

Directions Section

Directions

Wipe injection site vigorously and discard

Other Information Section

Other information

Store at room temperature: 15 degrees C - 30 degrees C (59-86 degrees F)

Inactive Ingredient Section

Inactive ingredients

purified water

Package Label

NDC 67752-0001-1 AMSINO AMSure Alcohol Prep Pad Prep pad size 1-1/5"x1-1/5" REF APP001S

STERILE DO NOT REUSE LATEX FREE

Distributed by: Amsino International, Inc. 855 Towne Center Dr., Pomona, CA 91767, USA

AMSure is a registered trademark of Amisino International, Inc. L5666 Rev. A

TEAR HERE